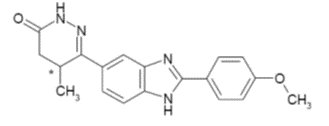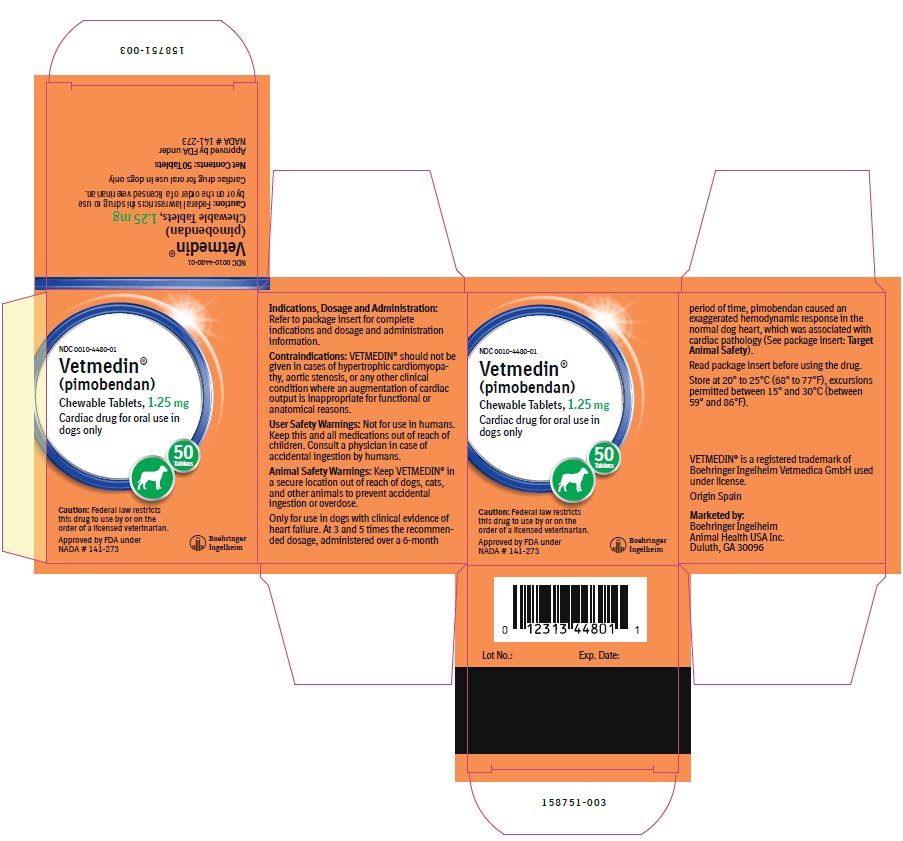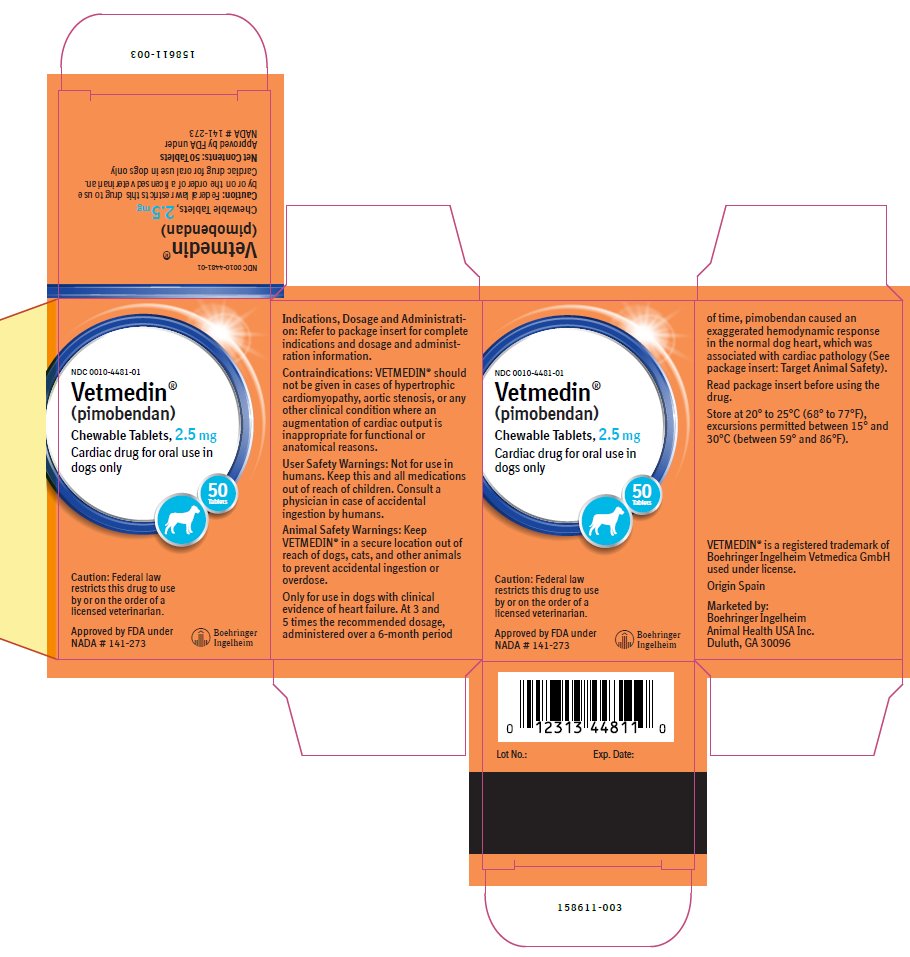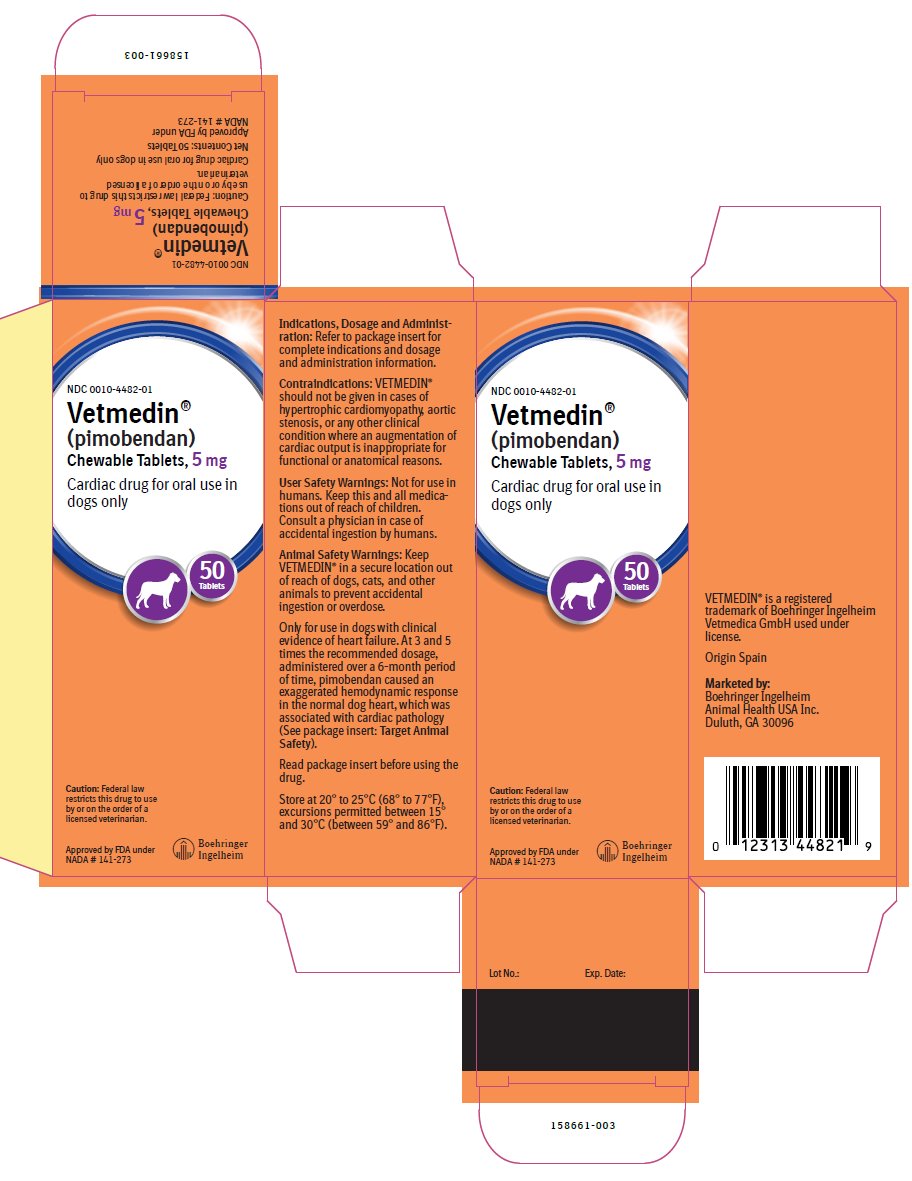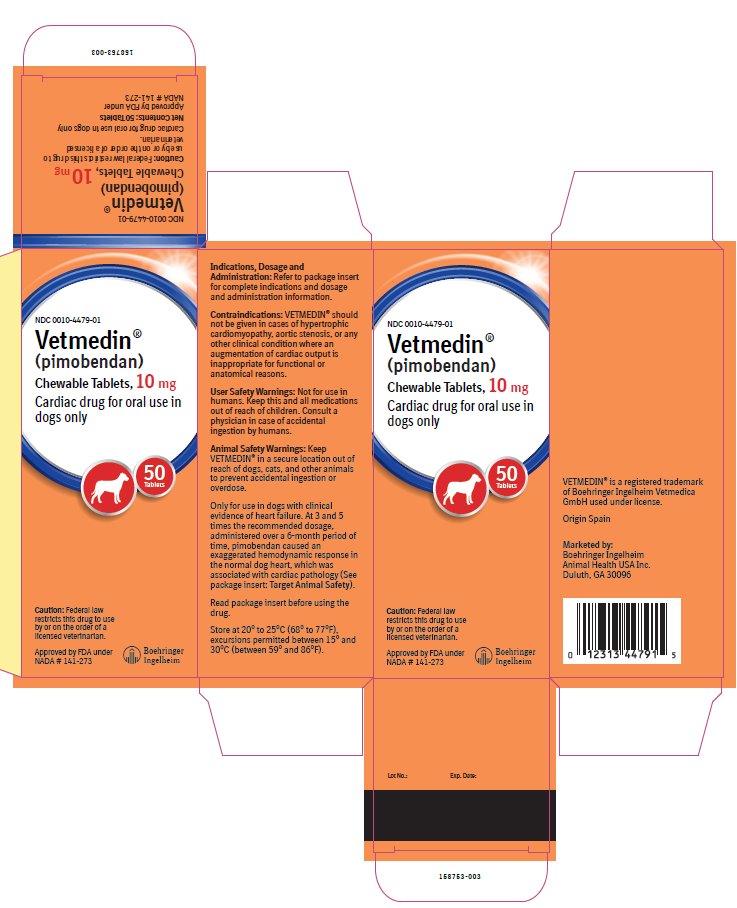 DRUG LABEL: Vetmedin
NDC: 0010-4480 | Form: TABLET, CHEWABLE
Manufacturer: Boehringer Ingelheim Animal Health USA Inc.
Category: animal | Type: PRESCRIPTION ANIMAL DRUG LABEL
Date: 20250221

ACTIVE INGREDIENTS: PIMOBENDAN 1.25 mg/1 1

Vetmedin® (pimobendan)
Chewable Tablets

Cardiac drug for oral use in dogs only

Caution:

Federal law restricts this drug to use by or on the order of a licensed veterinarian.

Description:

VETMEDIN (pimobendan) is supplied as oblong half-scored chewable tablets containing 1.25, 2.5, 5 or 10 mg pimobendan per tablet. Pimobendan, a benzimidazole-pyridazinone derivative, is a nonsympathomimetic, non-glycoside inotropic drug with vasodilatative properties. Pimobendan exerts a stimulatory myocardial effect by a dual mechanism of action consisting of an increase in calcium sensitivity of cardiac myofilaments and inhibition of phosphodiesterase (Type III). Pimobendan exhibits vasodilating activity by inhibiting phosphodiesterase III activity. The chemical name of pimobendan is 4,5-dihydro-6-[2-(4-methoxyphenyl)-1H-benzimidazole-5-yl]-5-methyl-3(2H)-pyridazinone. The structural formula of pimobendan is:

Indications:

VETMEDIN (pimobendan) is indicated for the management of the signs of mild, moderate, or severe congestive heart failure in dogs due to clinical myxomatous mitral valve disease (MMVD) or dilated cardiomyopathy (DCM). VETMEDIN is indicated for use with concurrent therapy for congestive heart failure (e.g.,furosemide, etc.) as appropriate on a case-by-case basis.

Dosage and Administration:

VETMEDIN should be administered orally at a total daily dose of 0.23 mg/lb (0.5 mg/kg) body weight, using a suitable combination of whole or half tablets. The total daily dose should be divided into 2 portions that are not necessarily equal, and the portions should be administered approximately 12 hours apart (i.e., morning and evening). The tablets are scored and the calculated dosage should be provided to the nearest half tablet increment.

Contraindications:

VETMEDIN should not be given in cases of hypertrophic cardiomyopathy, aortic stenosis, or any other clinical condition where an augmentation of cardiac output is inappropriate for functional or anatomical reasons.

Warnings:

User Safety Warnings: Not for use in humans. Keep this and all medications out of reach of children. Consult a physician in case of accidental ingestion by humans.

Animal Safety Warnings: Keep VETMEDIN in a secure location out of reach of dogs, cats, and other animals to prevent accidental ingestion or overdose.

Only for use in dogs with clinical evidence of heart failure. At 3 and 5 times the recommended dosage, administered over a 6-month period of time, pimobendan caused an exaggerated hemodynamic response in the normal dog heart, which was associated with cardiac pathology (See Target Animal Safety).

Precautions:

The safety of VETMEDIN has not been established in dogs with asymptomatic heart disease or in heart failure caused by etiologies other than MMVD or DCM. The safe use of VETMEDIN has not been evaluated in dogs younger than 6 months of age, dogs with congenital heart defects, dogs with diabetes mellitus or other serious metabolic diseases, dogs used for breeding, or pregnant or lactating bitches.

Adverse Reactions:

Pre-Approval Experience: Clinical findings/adverse reactions were recorded in a 56-day field study of dogs with congestive heart failure (CHF) due to MMVD (256 dogs) or DCM (99 dogs). Dogs were treated with either VETMEDIN (175 dogs) or the active control enalapril maleate (180 dogs). Dogs in both treatment groups received additional background cardiac therapy (See Effectiveness for details and the difference in digoxin administration between treatment groups).

The VETMEDIN group had the following prevalence (percent of dogs with at least one occurrence) of common adverse reactions/new clinical findings (not present in a dog prior to beginning study treatments): poor appetite (38%), lethargy (33%), diarrhea (30%), dyspnea (29%), azotemia (14%), weakness and ataxia (13%), pleural effusion (10%), syncope (9%), cough (7%), sudden death (6%), ascites (6%), and heart murmur (3%). Prevalence was similar in the active control group. The prevalence of renal failure was higher in the active control group (4%) compared to the VETMEDIN group (1%).

Adverse reactions/new clinical findings were seen in both treatment groups and were potentially related to CHF, the therapy of CHF, or both. The following adverse reactions/new clinical findings are listed according to body system and are not in order of prevalence: CHF death, sudden death, chordae tendineae rupture, left atrial tear, arrhythmias overall, tachycardia, syncope, weak pulses, irregular pulses, increased pulmonary edema, dyspnea, increased respiratory rate, coughing, gagging, pleural effusion, ascites, hepatic congestion, decreased appetite, vomiting, diarrhea, melena, weight loss, lethargy, depression, weakness, collapse, shaking, trembling, ataxia, seizures, restlessness, agitation, pruritus, increased water consumption, increased urination, urinary accidents, azotemia, dehydration, abnormal serum electrolyte, protein, and glucose values, mild increases in serum hepatic enzyme levels, and mildly decreased platelet counts.

See Table 1 for mortality due to CHF (including euthanasia, natural death, and sudden death) and for the development of new arrhythmias (not present in a dog prior to beginning study treatments) by treatment group and type of heart disease (MMVD or DCM) in the 56-day field study.

Table 1: CHF Death and New Arrhythmias in the 56-Day Field Study

 | VETMEDIN® Group | Active Control Group
Dogs that died due to CHF | 14.3%; n = 175; 9 of 126 dogs with MMVD; 16 of 49 dogs with DCM | 14.4%; n = 180; 16 of 130 dogs with MMVD; 10 of 50 dogs with DCM
Dogs that developed new arrhythmiasa | 39.4%; n = 175; 45 of 126 dogs with MMVD; 24 of 49 dogs with DCM | 45.0%; n = 180; 59 of 130 dogs with MMVD; 22 of 50 dogs with DCM

a New arrhythmias included supraventricular premature beats and tachycardia, atrial fibrillation, atrioventricular block, sinus bradycardia, ventricular premature beats and tachycardia, and bundle branch block.

Following the 56-day masked field study, 137 dogs in the VETMEDIN group were allowed to continue on VETMEDIN in an open-label extended-use study without restrictions on concurrent therapy. The adverse reactions/new clinical findings in the extended-use study were consistent with those reported in the 56-day study, with the following exception: One dog in the extended-use study developed acute cholestatic liver failure after 140 days on VETMEDIN and furosemide.

Post-Approval Experience (2023): The following adverse events are based on post-approval adverse drug experience reporting for VETMEDIN. Not all adverse events are reported to FDA/CVM. It is not always possible to reliably estimate the adverse event frequency or establish a causal relationship to product exposure using these data.

The following adverse events reported in dogs, are listed in decreasing order of reporting frequency:

Diarrhea, lethargy, anorexia, emesis, cough, tachycardia, ataxia, dyspnea, convulsion, elevated liver enzymes (ALT, ALP), increased BUN and/or creatinine, tremors, hyperactivity, pruritus, syncope, allergic reactions (including allergic edema/facial edema, erythema, and hives), hypotension, hypertension, coagulation abnormalities (including thrombocytopenia, hemorrhage and petechia), and hyperglycemia (with or without diabetes mellitus). Death has been reported in some cases.

Contact Information: To report suspected adverse reactions, to obtain a Safety Data Sheet (SDS), or for technical assistance, contact Boehringer Ingelheim Animal Health USA Inc. at 1-888-637-4251. For additional information about adverse drug experience reporting for animal drugs, contact the FDA at 1-888-FDA-VETS or at www.fda.gov/reportanimalae.

Clinical Pharmacology:

Pimobendan is oxidatively demethylated to a pharmacologically active metabolite which is then conjugated with sulfate or glucuronic acid and excreted mainly via feces. The mean extent of protein binding of pimobendan and the active metabolite in dog plasma is >90%. Following a single oral administration of 0.25 mg/kg VETMEDIN tablets the maximal mean (± 1 SD) plasma concentrations (Cmax) of pimobendan and the active metabolite were 3.09 (0.76) ng/mL and 3.66 (1.21) ng/mL, respectively. Individual dog Cmax values for pimobendan and the active metabolite were observed 1 to 4 hours post-dose (mean: 2 and 3 hours, respectively). The total body clearance of pimobendan was approximately 90 mL/min/kg, and the terminal elimination half-lives of pimobendan and the active metabolite were approximately 0.5 hours and 2 hours, respectively. Plasma levels of pimobendan and active metabolite were below quantifiable levels by 4 and 8 hours after oral administration, respectively. The steady-state volume of distribution of pimobendan is 2.6 L/kg indicating that the drug is readily distributed into tissues. Food decreased the bioavailability of an aqueous solution of pimobendan, but the effect of food on the absorption of pimobendan from VETMEDIN tablets is unknown.

In normal dogs instrumented with left ventricular (LV) pressure transducers, pimobendan increased LV dP/dtmax (a measure of contractility of the heart) in a dose dependent manner between 0.1 and 0.5 mg/kg orally. The effect was still present 8 hours after dosing. There was a delay between peak blood levels of pimobendan and active metabolite and the maximum physiologic response (peak LV dP/dtmax). Blood levels of pimobendan and active metabolite began to drop before maximum contractility was seen. Repeated oral administration of pimobendan did not result in evidence of tachyphylaxis (decreased positive inotropic effect) or drug accumulation (increased positive inotropic effect). Laboratory studies indicate that the positive inotropic effect of pimobendan may be attenuated by the concurrent use of a β-adrenergic blocker or a calcium channel blocker.

Effectiveness:

In a double-masked, multi-site, 56-day field study, 355 dogs with modified New York Heart Association‡ (NYHA) Class II, III, or IV CHF due to MMVD or DCM were randomly assigned to either the active control (enalapril maleate) or the VETMEDIN (pimobendan) treatment group. Of the 355 dogs, 52% were male and 48% were female; 72% were diagnosed with MMVD and 28% were diagnosed with DCM; 34% had Class II, 47% had Class III, and 19% had Class IV CHF. Dogs ranged in age and weight from 1 to 17 years and 3.3 to 191 lbs, respectively. The most common breeds were mixed breed, Doberman Pinscher, Cocker Spaniel, Miniature/Toy Poodle, Maltese, Chihuahua, Miniature Schnauzer, Dachshund, and Cavalier King Charles Spaniel. The 180 dogs (130 MMVD, 50 DCM) in the active control group received enalapril maleate (0.5 mg/kg once or twice daily), and all but 2 received furosemide. Per protocol, all dogs with DCM in the active control group received digoxin. The 175 dogs (126 MMVD, 49 DCM) in the VETMEDIN group received pimobendan (0.5 mg/kg/day divided into 2 portions that were not necessarily equal, and the portions were administered approximately 12 hours apart), and all but 4 received furosemide. Digoxin was optional for treating supraventricular tachyarrhythmia in either treatment group, as was the addition of a b-adrenergic blocker if digoxin was ineffective in controlling heart rate. After initial treatment at the clinic on Day 1, dog owners were to administer the assigned product and concurrent medications for up to 56±4 days.

The determination of effectiveness (treatment success) for each case was based on improvement in at least 2 of the 3 following primary variables: modified NYHA classification, pulmonary edema score by a

masked veterinary radiologist, and the investigator’s overall clinical effectiveness score (based on physical examination, radiography, electrocardiography, and clinical pathology). Attitude, pleural effusion, coughing, activity level, furosemide dosage change, cardiac size, body weight, survival, and owner observations were secondary evaluations contributing information supportive to product effectiveness and safety.

Based on protocol compliance and individual case integrity, 265 cases (134 VETMEDIN, 131 active control) were evaluated for treatment success on Day 29. See Table 2 for effectiveness results.

Table 2: Effectiveness Results for the 56-Day Field Study
 | VETMEDIN® Group | Active Control Group
Treatment Success on Day 29 | 80.7%; n = 134; 88 of 101 dogs with MMVD; 20 of 33 dogs with DCM | 76.3%; n = 131; 77 of 100 dogs with MMVD; 23 of 31 dogs with DCM
Treatment Success on Day 56 | 71.1%; n = 113; 66 of 85 dogs with MMVD; 13 of 28 dogs with DCM | 67.2%; n = 110; 56 of 85 dogs with MMVD; 17 of 25 dogs with DCM
No increase in furosemide dose between Day 1 and Day 29 | 78.3%; n = 130 | 68.6%; n = 126

At the end of the 56-day study, dogs in the VETMEDIN group were enrolled in an unmasked field study to monitor safety under extended use, without restrictions on concurrent medications.

VETMEDIN was used safely in dogs concurrently receiving furosemide, digoxin, enalapril, atenolol, spironolactone, nitroglycerin, hydralazine, diltiazem, antiparasitic products (including heartworm disease prevention), antibiotics (metronidazole, cephalexin, amoxicillin-clavulanate, fluoroquinolones), topical ophthalmic and otic products, famotidine, theophylline, levothyroxine sodium, diphenhydramine, hydrocodone, metoclopramide, and butorphanol, and in dogs on sodium-restricted diets.

‡The modified NYHA classification was historically used to stage dogs with heart disease.

A dog with modified NYHA Class II heart failure has fatigue, shortness of breath, coughing, etc. apparent when ordinary exercise is exceeded.

A dog with modified NYHA Class III heart failure is comfortable at rest, but exercise capacity is minimal.

A dog with modified NYHA Class IV heart failure has no capacity for exercise and disabling clinical signs are present even at rest.

Palatability:

In a laboratory study, the palatability of VETMEDIN was evaluated in 20 adult female Beagle dogs offered doses twice daily for 14 days. Ninety percent (18 of 20 dogs) voluntarily consumed more than 70% of the 28 tablets offered. Including two dogs that consumed only 4 and 7% of the tablets offered, the average voluntary consumption was 84.2%.

Target Animal Safety:

In a laboratory study, VETMEDIN chewable tablets were administered to 6 healthy Beagles per treatment group at 0 (control), 1, 3, and 5 times the recommended dosage for 6 months. See Table 3 for cardiac pathology results. The cardiac pathology/histopathology noted in the 3X and 5X dose groups is typical of positive inotropic and vasodilator drug toxicity in normal dog hearts, and is associated with exaggerated hemodynamic responses to these drugs. None of the dogs developed signs of heart failure and there was no mortality.

Table 3: Incidence of Cardiac Pathology/Histopathology in the Six-month Safety Study

Severe left ventricular hypertrophy with multifocal subendocardial ischemic lesions | One 3X and two 5X dogsa
Moderate to marked myxomatous thickening of the mitral valves | Three 5X dogs
Myxomatous thickening of the chordae tendineae | One 3X and two 5X dogs
Endocardial thickening of the left ventricular outflow tract | One 1X, two 3X, and two 5X dogs
Left atrial endocardial thickening (jet lesions) in 2 of the dogs that developed murmurs of mitral valve insufficiency | One 3X and one 5X dog
Granulomatous inflammatory lesion in the right atrial myocardium | One 3X dog

a Most of the gross and histopathologic findings occurred in these three dogs

Murmurs of mitral valve insufficiency were detected in one 3X (Day 65) and two 5X dogs (Days 135 and 163). These murmurs (grades II-III of VI) were not associated with clinical signs.

Indirect blood pressure was unaffected by VETMEDIN at the label dose (1X). Mean diastolic blood pressure was decreased in the 3X group (74 mmHg) compared to the control group (82 mmHg). Mean systolic blood pressure was decreased in the 5X group (117 mmHg) compared to the control group (124 mmHg). None of the dogs had clinical signs of hypotension.

On 24-hour Holter monitoring, mean heart rate was increased in the 5X group (101 beats/min) compared to the control group (94 beats/min). Not counting escape beats, the 3X and 5X groups had slightly higher numbers of isolated ventricular ectopic complexes (VEs). The maximum number of non-escape VEs recorded either at baseline or in a control group dog was 4 VEs/24 hours. At either Week 4 or Week 20, three 3X group dogs had maximums of 33, 13, and 10 VEs/24 hours, and two 5X group dogs had maximums of 22 and 9 VEs/24 hours. One 1X group dog with no VEs at baseline had 6 VEs/24 hours at Week 4 and again at Week 20. Second-degree atrioventricular heart block was recorded in one 3X group dog at Weeks 4 and 20, and in one dog from each of the 1X and 5X groups at Week 20. None of the dogs had clinical signs associated with these electrocardiogram changes.

Treatment was associated with small differences in mean platelet counts (decreased in the 3X and 1X groups), potassium (increased in the 5X group), glucose (decreased in the 1X and 3X groups), and maximum blood glucose in glucose curves (increased in the 5X group). All individual values for these variables were within the normal range. Three 1X and one 5X group dogs had mild elevations of alkaline phosphatase (less than two times normal).

Loose stools and vomiting were infrequent and self-limiting.

Storage Information:

Store at 20° to 25°C (68° to 77°F), excursions permitted between 15° and 30°C (between 59° and 86°F).

How Supplied:

VETMEDIN® (pimobendan) Chewable Tablets:

Available as 1.25, 2.5, 5 and 10 mg oblong half-scored chewable tablets - 50 tablets per bottle.

NDC 0010-4480-01 - 1.25 mg - 50 tablets

NDC 0010-4482-01 - 5 mg - 50 tablets

NDC 0010-4481-01 - 2.5 mg - 50 tablets

NDC 0010-4479-01 - 10 mg - 50 tablets

Approved by FDA under NADA # 141-273

Marketed by:

Boehringer Ingelheim Animal Health USA Inc.

Duluth, GA 30096

VETMEDIN® is a registered trademark of Boehringer Ingelheim Vetmedica GmbH used under license.

© 2023 Boehringer Ingelheim Animal Health USA Inc.

All rights reserved.

Revised 06/2023

159637-004

Principal Display Panel – Display Carton, 1.25 mg, 50 Tablets

NCD 0010-4480-01

Vetmedin®

(pimobendan)

Chewable Tablets, 1.25 mg

Cardiac drug for oral use in dogs only.

50 Tablets

Caution: Federal law restricts this drug to use by or on the order of a licensed veterinarian.

Approved by FDA under NADA # 141-273

Principal Display Panel – Display Carton, 2.5 mg, 50 Tablets

NDC 0010-4481-01

Vetmedin®

(pimobendan)

Chewable Tablets, 2.5 mg

Cardiac drug for oral use in dogs only

50 Tablets

Caution: Federal law restricts this drug to use by or on the order of a licensed veterinarian.

Approved by FDA under NADA # 141-273

Principal Display Panel – Display Carton, 5 mg, 50 Tablets

NDC 0010-4482-01

Vetmedin®

(pimobendan)

Chewable Tablets, 5 mg

Cardiac drug for oral use in dogs only.

50 Tablets

Caution: Federal law restricts this drug to use by or on the order of a licensed veterinarian.

Approved by FDA under NADA # 141-273

Principal Display Panel - Display Carton, 10 mg, 50 Tablets

NDC 0010-4479-01

Vetmedin®

(pimobendan)

Chewable Tablets, 10 mg

Cardiac drug for oral use in dogs only.

50 Tablets

Caution: Federal law restricts this drug to use by or on the order of a licensed veterinarian.

Approved by FDA under NADA # 141-273